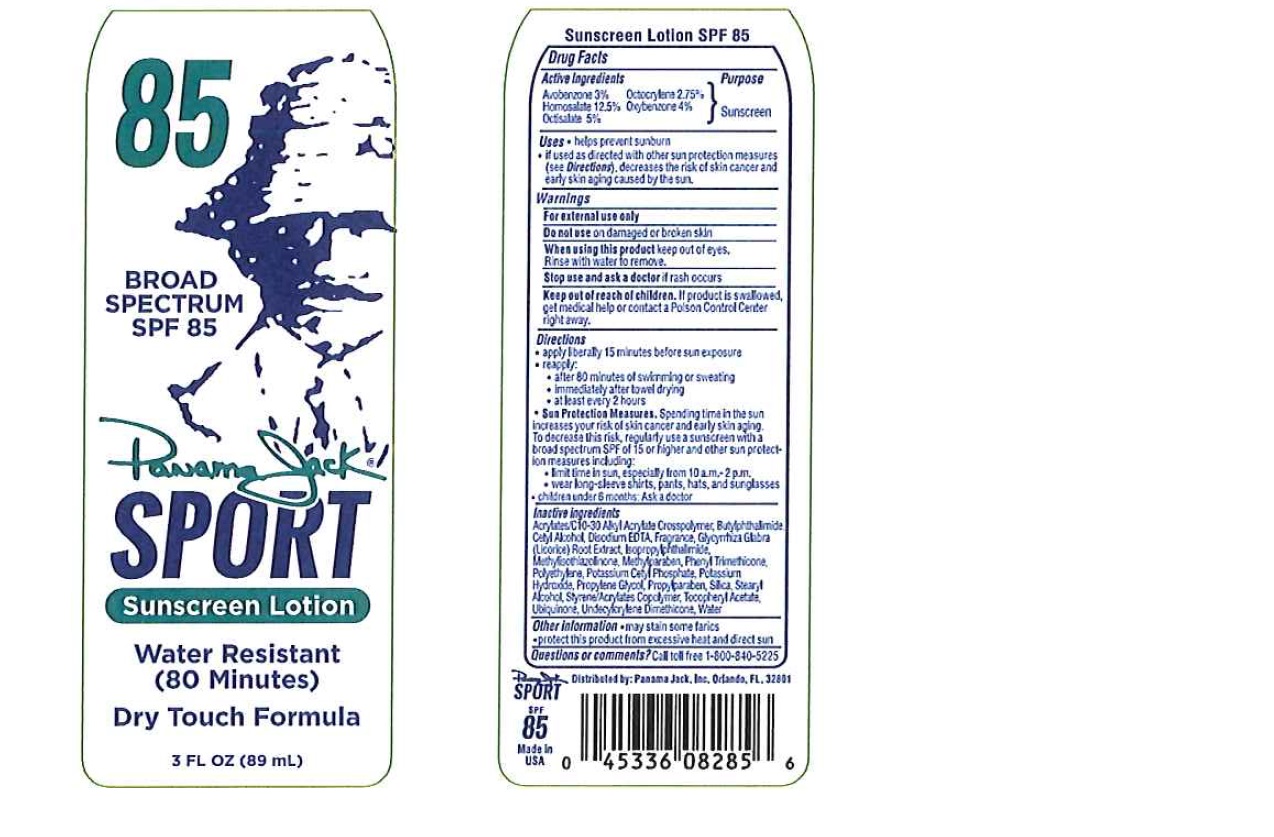 DRUG LABEL: Panama Jack
NDC: 58443-0221 | Form: SPRAY
Manufacturer: Prime Enterprises Inc.
Category: otc | Type: HUMAN OTC DRUG LABEL
Date: 20200117

ACTIVE INGREDIENTS: OXYBENZONE 38.8 mg/1 mL; AVOBENZONE 29.1 mg/1 mL; HOMOSALATE 121.25 mg/1 mL; OCTISALATE 48.5 mg/1 mL; OCTOCRYLENE 26.68 mg/1 mL
INACTIVE INGREDIENTS: SILICON DIOXIDE; LICORICE; EDETATE DISODIUM; HIGH DENSITY POLYETHYLENE; STEARYL ALCOHOL; METHYLISOTHIAZOLINONE; ISOPROPYLPHTHALIMIDE; UBIQUINONE Q2; PHENYL TRIMETHICONE; POTASSIUM CETYL PHOSPHATE; POTASSIUM HYDROXIDE; PROPYLENE GLYCOL; N-BUTYLPHTHALIMIDE; METHYLPARABEN; (C10-C30)ALKYL METHACRYLATE ESTER; STYRENE/ACRYLAMIDE COPOLYMER (MW 500000); ALPHA-TOCOPHEROL ACETATE; PROPYLPARABEN; WATER; CETYL ALCOHOL

Panama Jack Sport SPF 85 Dry Touch Sunscreen

Active Ingredients

Avobenzone 3%

Homosalate 12.5%

Octisalate 5%

Octocrylene 2.75%

Oxybenzone 4%

Purpose

Sunscreen

Uses

- helps prevent sunburn
- if used as directed with other sun protection measures (see Directions), decreases the risk of skin cancer and early skin aging caused by the sun.

WARNINGS

For external use only.

Do not use on damaged or broken skin

When using this product keep out of eyes. Rinse with water to remove.

Stop use and ask a doctor if rash occurs

Keep out of reach of children. If product is swallowed, get medical help or contact a Poison Control Center right away.

Directions

- apply liberally 15 minutes before sun exposure
- reapply:
- after 80 minutes of swimming or sweating
- immediately after towel drying
- at least every 2 hours
- Sun Protection Measures. Spending time in the sun increases your risk of skin cancer and early skin aging. To decrease this risk, regularly use a sunscreen with broad spectrum SPF of 15 or higher and other sun protection measures including:
- limit time in the sun, especially from 10 a.m. – 2 p.m.
- wear long-sleeve shirts, pants, hats, and sunglasses
- children under 6 months: Ask a doctor

INACTIVE INGREDIENT

Acrylates/C10-30 Alkyl Acrylate Crosspolymer, Butylphthalimide, Cetyl Alcohol, Disodium EDTA, Fragrance, Glycyrrhiza Glabra (Licorice) Root Extract, Isopropylphthalimide, Methylisothiazolinone, Methylparaben, Phenyl Trimethicone, Polyethylene, Potassium Cetyl Phosphate, Potassium Hydroxide, Propylene Glycol, Propylparaben, Silica, Stearyl Alcohol, Styrene/Acrylates Copolymer, Tocopheryl Acetate, Ubiquinone, Undecylcrylene Dimethicone, Water

Other Information

- may stain some fabrics
- protect this product from excessive heat and direct sun

Questions or Comments?

Call toll free 1-800-840-5225